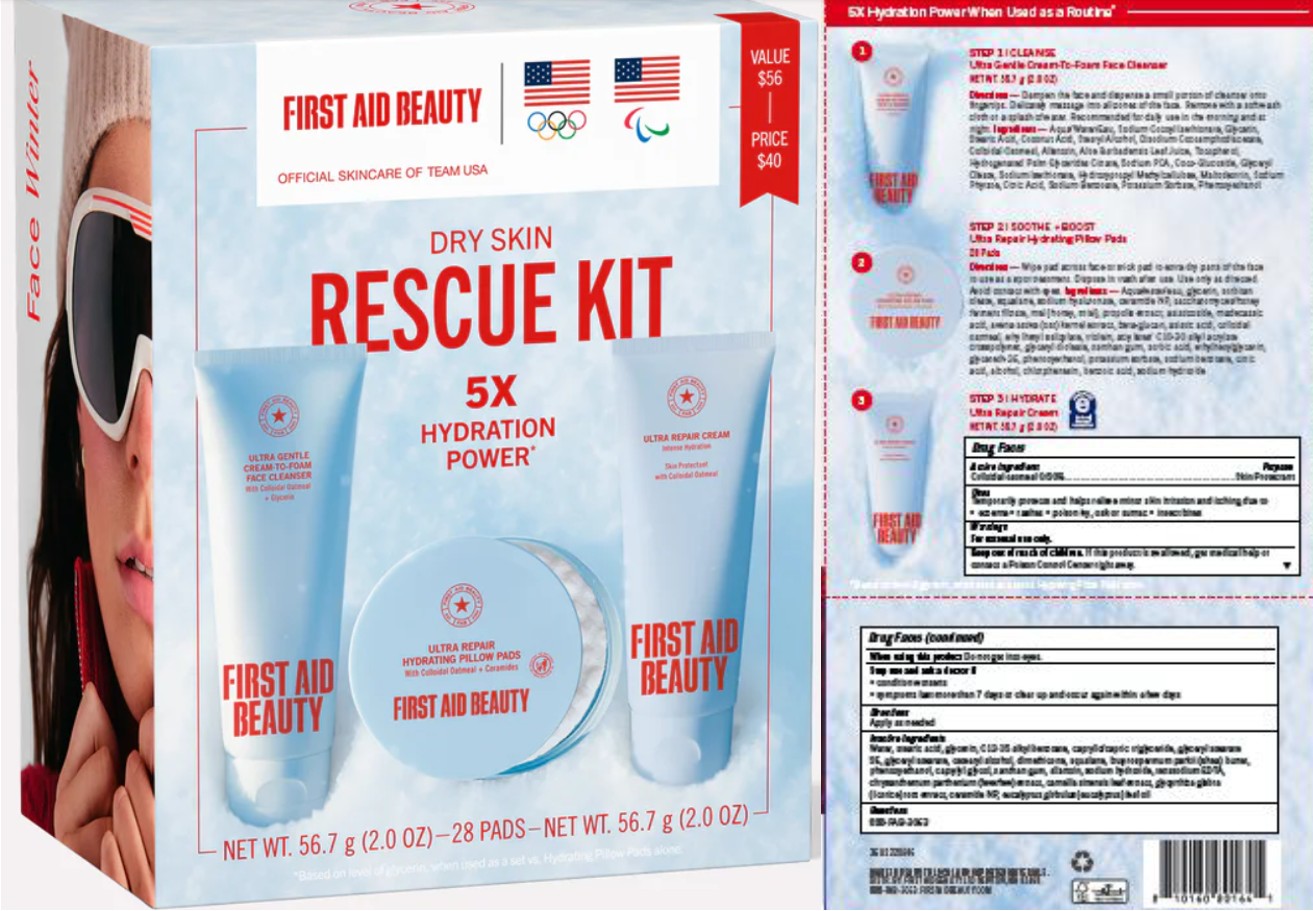 DRUG LABEL: First Aid Beauty Dry Skin Rescue Kit
NDC: 84126-220 | Form: KIT | Route: TOPICAL
Manufacturer: The Procter & Gamble Manufacturing Company
Category: otc | Type: HUMAN OTC DRUG LABEL
Date: 20260211

ACTIVE INGREDIENTS: OATMEAL 0.5 g/100 g
INACTIVE INGREDIENTS: WATER; C12-15 ALKYL BENZOATE; CAPRYLYL GLYCOL; BUTYROSPERMUM PARKII (SHEA) BUTTER; PHENOXYETHANOL; GLYCERIN; ALLANTOIN; GLYCERYL STEARATE; GLYCYRRHIZA GLABRA (LICORICE) ROOT POWDER; CERAMIDE NP; DIMETHICONE; STEARIC ACID; TANACETUM PARTHENIUM WHOLE; CETEARYL ALCOHOL; SQUALANE; GLYCERYL STEARATE SE; SODIUM HYDROXIDE; EUCALYPTUS GLOBULUS LEAF OIL; XANTHAN GUM; CAPRYLIC/CAPRIC TRIGLYCERIDE; TETRASODIUM EDTA; CAMELLIA SINENSIS LEAF

First Aid Beauty Dry Skin Rescue Kit

Drug Facts

Active ingredient

Colloidal Oatmeal 0.5%

Purpose

Skin Protectant

Uses

Temporarily protects and helps relieve minor skin irritation and itching due to exzema rashes poison ivy, oak or sumac insect bites

Warnings

For external use only.

KEEP OUT OF REACH OF CHILDREN

If swallowed, get medical help or contact Poison Control Center right away.

When using this product Do not get into eyes

Stop use and ask a doctor if

- condition worsens
- symptoms last more than 7 days or clear up and occur again within a few days

Directions

Apply as needed

Inactive ingredients

Water, stearic acid, glycerin, C12-15 alkyl benzoate, caprylic/capric triglyceride, glyceryl stearate SE, glyceryl stearate, cetearyl alcohol, dimethicone, squalane, butyrospermum parkii (shea) butter, phenoxyethanol, caprylyl glycol, xanthan gum, allantoin, sodium hydroxide, tetrasodium EDTA, chrysanthemum parthenium (feverfew) extract, camellia sinensis leaf extract, glycyrrhiza glabra (licorice) root extract, ceramide NP, eucalyptus globulus (eucalyptus) leaf oil

Questions:

888-FAB-3063

MADE IN USA

FIRST AID BEAUTY LTD

NEWTON, MA 02458

WWW.FIRSTAIDBEAUTY.COM

PRINCIPAL DISPLAY PANEL - Carton

FIRST AID BEAUTY

OFFICIAL SKINCARE OF TEAM USA

DRY SKIN

RESCUE KIT

5X

HYDRATION

POWER

FIRST AID BEAUTY ULTRA GENTLE CREAM TO FOAM FACE CLEANSER

FIRST AID BEAUTY ULTRA REPAIR HYDRATING PILLOW PADS

FIRST AID BEAUTY ULTRA REPAIR CREAM INTENSE HYDRATION

NET WT 56.7 g (2.0 OZ) - 28 PADS - NET WT. 56.7 g (2.0 OZ)